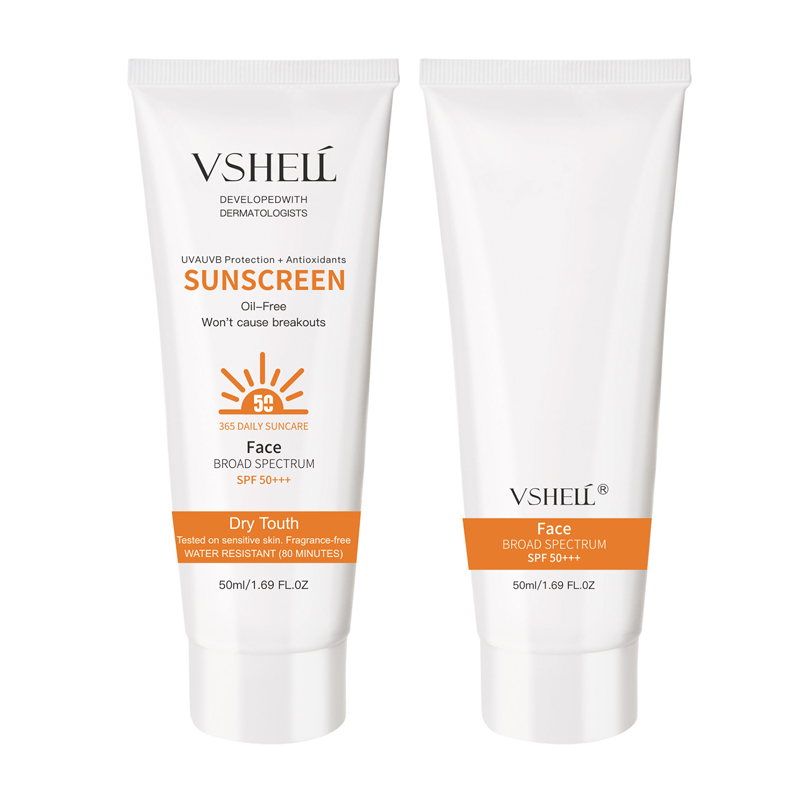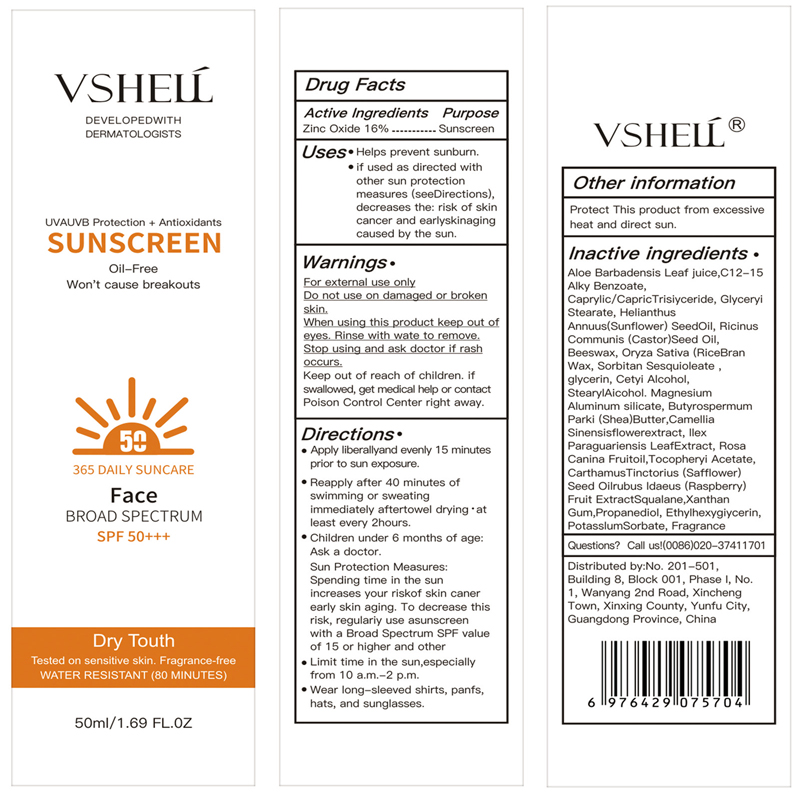 DRUG LABEL: VSHELL SUNSCREEN
NDC: 84507-006 | Form: CREAM
Manufacturer: Guangdong Miaolian Cosmetics Co., Ltd.
Category: otc | Type: HUMAN OTC DRUG LABEL
Date: 20240724

ACTIVE INGREDIENTS: ZINC OXIDE 16 g/100 g
INACTIVE INGREDIENTS: SHEA BUTTER; ALPHA-TOCOPHEROL ACETATE; PROPANEDIOL; CASTOR OIL; SORBITAN SESQUIOLEATE; CETYL ALCOHOL; GLYCERIN; POTASSIUM SORBATE; STEARYL ALCOHOL; GLYCERYL MONOSTEARATE; ALLYL BENZOATE; SQUALANE; MEDIUM-CHAIN TRIGLYCERIDES; MAGNESIUM ALUMINUM SILICATE; FRAGRANCE 13576; ILEX PARAGUARIENSIS LEAF; SUNFLOWER OIL; ROSA CANINA FRUIT OIL; CAMELLIA SINENSIS FLOWER; YELLOW WAX; XANTHAN GUM; ALOE VERA LEAF; RASPBERRY; ETHYLHEXYLGLYCERIN; SAFFLOWER SEED; RICE BRAN

Active Ingredient

Zinc Oxide 16%

Purpose

Helps prevent sunburn

Use

If used as directed with other sun protection measures （see Directions），decreases the risk of skin cancer and early skin aging caused by the sun.

Warnings

For external use only

Do not use on damaged or broken skin.

When Using

When using this product keep out of eyes.
Rinse with wate to remove.
Stop use and ask doctor if rash occurs.

Stop Use

Stop use and ask doctor if rash occurs

Ask Doctor

Not for use in children under 6 months old

Keep Oot Of Reach Of Children

Keep out of reach of children. Iiswallowed, get medical help orcontact Poison Control Center right away.

Directions

Apply liberally and evenly 15 minutes prior to sun exposure.Reapply after 40 minutes of swimming or sweating immediately aftertowel drying "at least every 2 hours.

Other information

Protect this product from excessive heat and direct sun.

Inactive Ingredients

Aloe Barbadensis Leaf Juice, C12-15 Alkyl Benzoate, Caprylic/Capric Triglyceride, Glyceryl Stearate, Helianthus Annuus (Sunflower) Seed Oil, Ricinus Communis (Castor) Seed Oil, Beeswax, Oryza Sativa (Rice) Bran Wax, Sorbitan Sesquioleate, Glycerin, Cetyl Alcohol, Stearyl Alcohol, Magnesium Aluminum Silicate, Butyrospermum Parkii (Shea) Butter, Camellia Sinensis Flower Extract, Ilex Paraguariensis Leaf Extract, Rosa Canina Fruit Oil, Tocopheryl Acetate, Carthamus Tinctorius (Safflower) Seed Oil, Rubus Idaeus (Raspberry) Fruit Extract, Squalane, Xanthan Gum, Propanediol, Ethylhexylglycerin, Potassium Sorbate, Fragrance

Questions

Call us！（0086）020-37411701